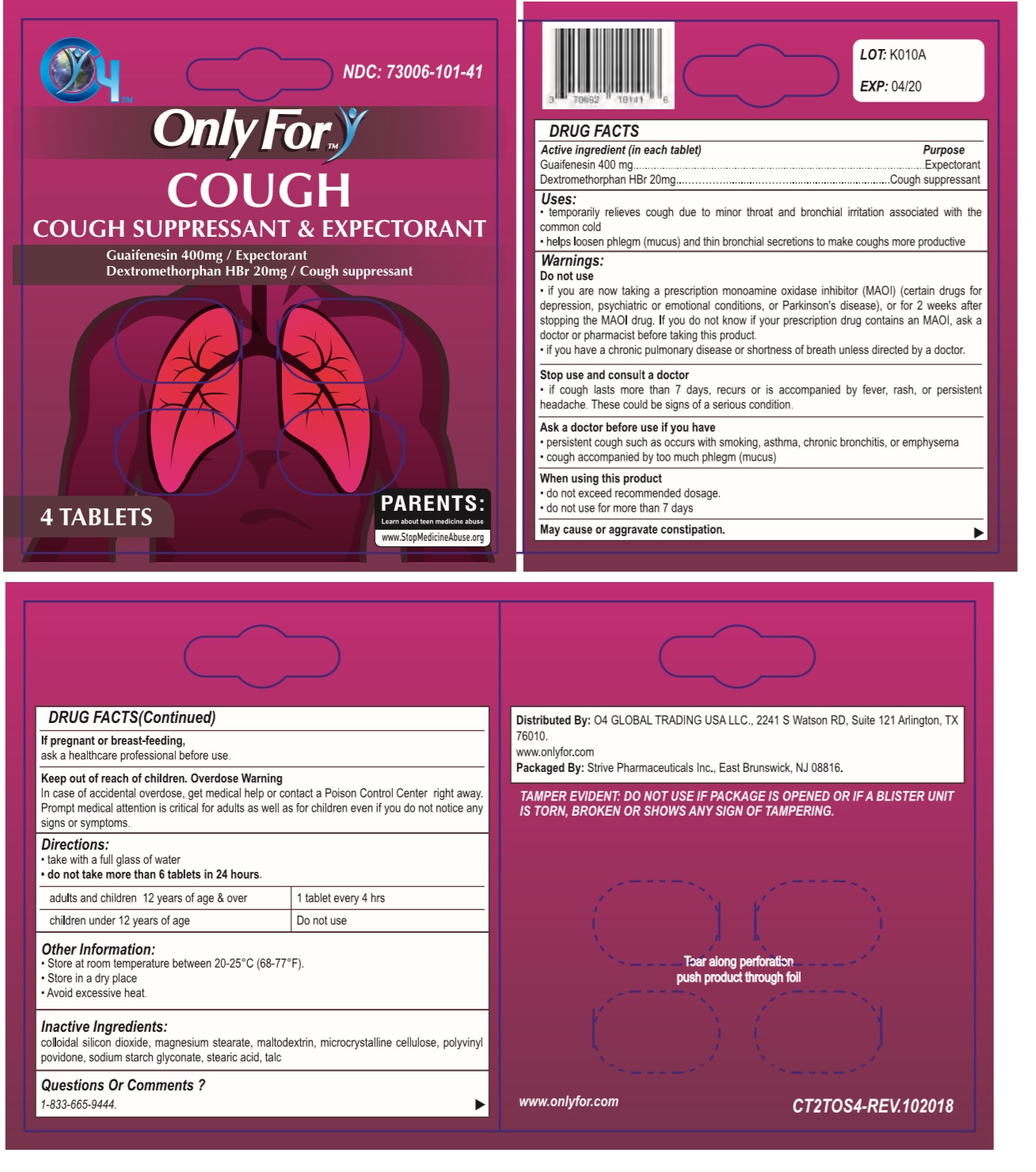 DRUG LABEL: Only For
NDC: 73006-101 | Form: TABLET
Manufacturer: O4 Global Trading Usa, Llc
Category: otc | Type: HUMAN OTC DRUG LABEL
Date: 20190528

ACTIVE INGREDIENTS: GUAIFENESIN 400 mg/1 1; DEXTROMETHORPHAN HYDROBROMIDE 20 mg/1 1
INACTIVE INGREDIENTS: SILICON DIOXIDE; MAGNESIUM PALMITOSTEARATE; MALTODEXTRIN; MICROCRYSTALLINE CELLULOSE 101; POVIDONE, UNSPECIFIED; SODIUM STARCH GLYCOLATE TYPE A POTATO; STEARIC ACID; TALC

Only For - COUGH

Active ingredient (in each tablet)

Guaifenesin 400 mg

Dextromethorphan HBr 20mg

Purpose

Expectorant

Cough suppressant

Uses:

• temporarily relieves cough due to minor throat and bronchial irritation associated with the common cold

• helps loosen phlegm (mucus) and thin bronchial secretions to make coughs more productive

Warnings:

Do not use

• if you are now taking a prescription monoamine oxidase inhibitor (MAOI) (certain drugs for depression, psychiatric or emotional conditions, or Parkinson's disease), or for 2 weeks after stopping the MAOI drug. If you do not know if your prescription drug contains an MAOI, ask a doctor or pharmacist before taking this product.

• if you have a chronic pulmonary disease or shortness of breath unless directed by a doctor.

Stop use and consult a doctor

• if cough lasts more than 7 days, recurs or is accompanied by fever, rash, or persistent headache. These could be signs of a serious condition.

Ask a doctor before use if you have

• persistent cough such as occurs with smoking, asthma, chronic bronchitis, or emphysema

• cough accompanied by too much phlegm (mucus)

When using this product

• do not exceed recommended dosage.

• do not use for more than 7 days

May cause or aggravate constipation.

If pregnant or breast-feeding,

ask a healthcare professional before use.

Keep out of reach of children. Overdose Warning

In case of accidental overdose, get medical help or contact a Poison Control Center right away. Prompt medical attention is critical for adults as well as for children even if you do not notice any signs or symptoms.

Directions:

- take with a full glass of water
- do not take more than 6 tablets in 24 hours.

adults and children 12 years of age & over | 1 tablet every 4 hrs
children under 12 years of age | Do not use

Other Information:

• Store at room temperature between 20-25°C (68-77°F).
• Store in a dry place
• Avoid excessive heat.

Inactive Ingredients:

colloidal silicon dioxide, magnesium stearate, maltodextrin, microcrystalline cellulose, polyvinyl povidone, sodium starch glyconate, stearic acid, talc

Questions Or Comments ?

1-833-665-9444.

NDC: 73006-101-41

Distributed By: O4 GLOBAL TRADING USA LLC., 2241 S Watson RD, Suite 121 Arlington, TX 76010.

www.onlyfor.com

Packaged By: Strive Pharmaceuticals Inc., East Brunswick, NJ 08816.

TAMPER EVIDENT: DO NOT USE IF PACKAGE IS OPENED OR IF A BLISTER UNIT IS TORN, BROKEN OR SHOWS ANY SIGN OF TAMPERING.

Tear along perforation push product through foil